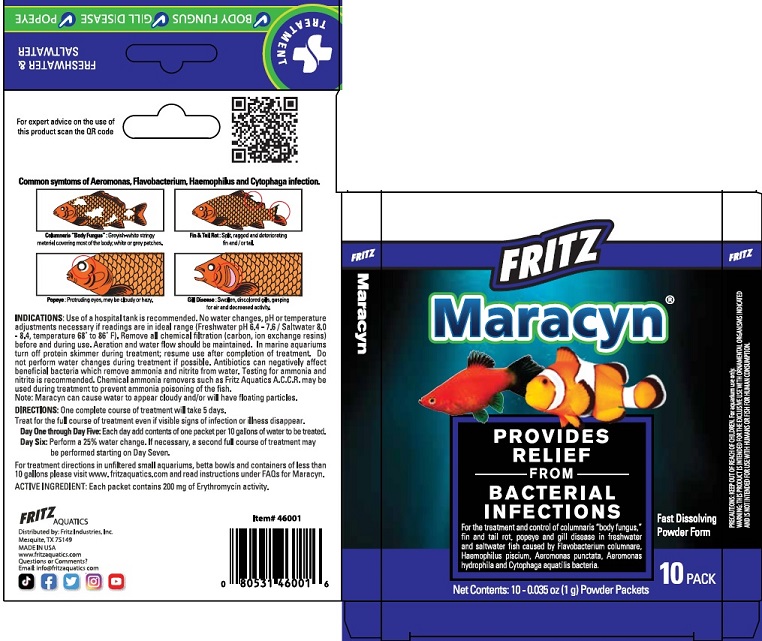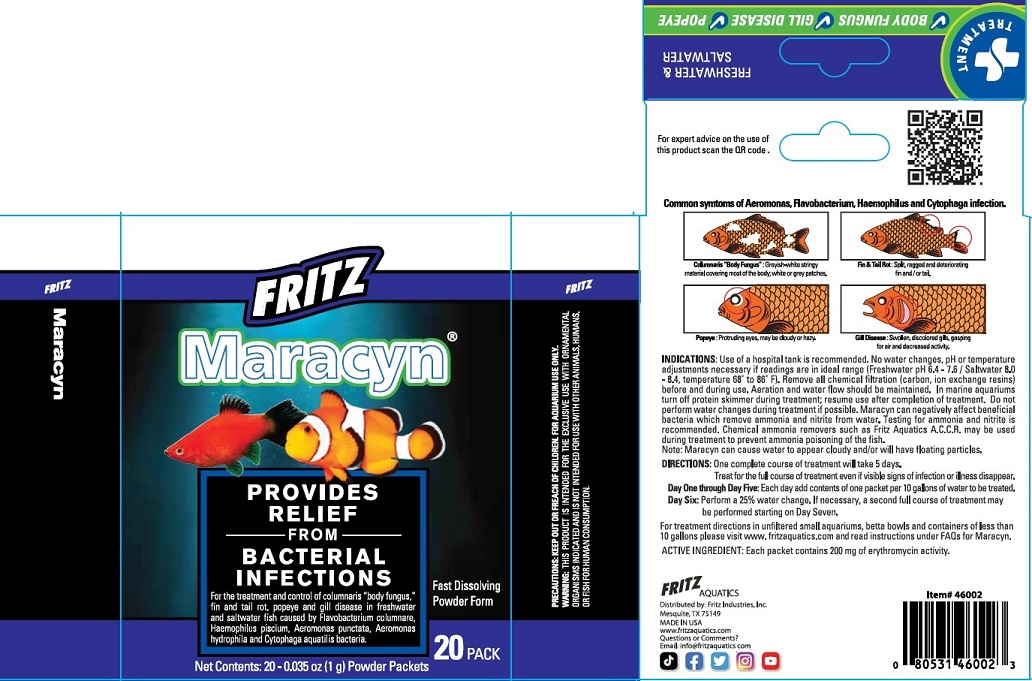 DRUG LABEL: Fritz Aquatics Mardel Maracyn
NDC: 53745-011 | Form: POWDER
Manufacturer: Fritz Industries
Category: animal | Type: OTC ANIMAL DRUG LABEL
Date: 20240108

ACTIVE INGREDIENTS: ERYTHROMYCIN PHOSPHATE 200 mg/0.6 g

FRITZ - Maracyn

ACTIVE INGREDIENT: Each packet contains 200 mg erythromycin activity.